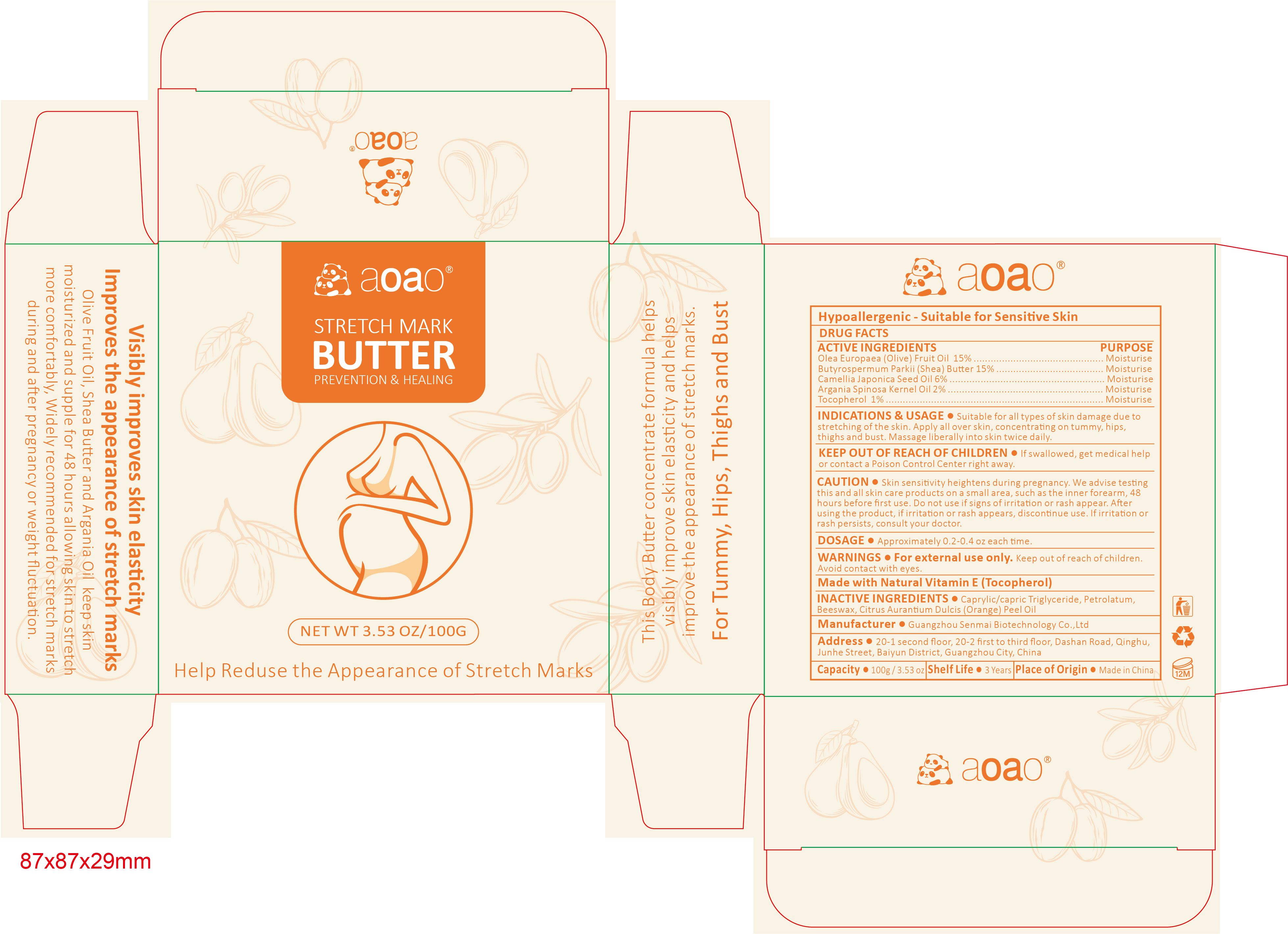 DRUG LABEL: AOAO STRETCH MARK BUTTER
NDC: 84509-022 | Form: CREAM
Manufacturer: Guangzhou Senmai Biotechnology Co.,Ltd
Category: otc | Type: HUMAN OTC DRUG LABEL
Date: 20241012

ACTIVE INGREDIENTS: OLIVE OIL 15000 mg/100 g; SHEA BUTTER 15000 mg/100 g; CAMELLIA JAPONICA SEED OIL 6000 mg/100 g; TOCOPHEROL 1000 mg/100 g; ARGAN OIL 2000 mg/100 g
INACTIVE INGREDIENTS: MEDIUM-CHAIN TRIGLYCERIDES; YELLOW WAX; ORANGE OIL; PETROLATUM

Active Ingredients

Olea Europaea (Olive) Fruit Oil 15%
Butyrospermum Parkii (Shea) Butter 15%
Camellia Japonica Seed Oil 6%
Argania Spinosa Kernel Oil 2%
Tocopherol 1%

Purpose

Moisturise

Uses

Suitable for all types of skin damage due to stretching of the skin. Apply all over skin, concentrating on tummy, hips,thighs and bust.Massage liberally into skin twice daily.

Warnings

For external use only. Keep out ofreach of children.Avoid contact with eyes

Keep out of reach of children.

If swallowed, get medical help or contact a Poison Control Center right away

CAUTION

Skin sensitivity heightens during pregnancy.We advise testing this and all skin care products on a small area, such as the inner forearm, 48 hours before first use.Do not use if signs of irritation or rash appear.After using the product, if irritation or rash appears,discontinue use.lf irritation or rash persists, consult your doctor.

DESCRIPTION

Made with Natural Vitamin E (Tocopherol)

Inactive Ingredients

Caprylic/capric Triglyceride, Petrolatum, Beeswax, Citrus Aurantium Dulcis (Orange) Peel Oil

Product Name

AOAO STRETCH MARK BUTTER

Manufacturer

Guangzhou Senmai Biotechnology Co.,Ltd

Address

20-1second floor, 20-2 first to third floor,Dashan Road,Qinghu,Junhe Street, Baiyun district, Guangzhou City, China.

Capacity

100g/3.53oz

DOSAGE

Approximately 02-0.4 fl.oz each time

Shelf Life

3 Years

Place of Origin

Made in China